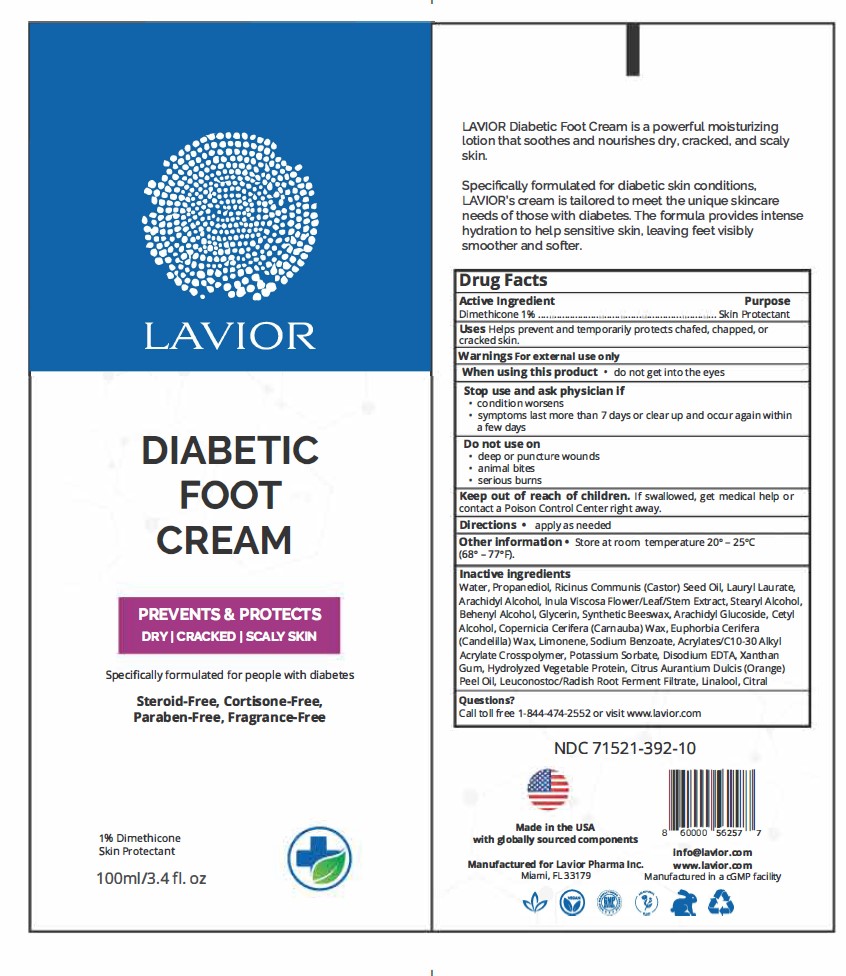 DRUG LABEL: Diabetic Foot Cream
NDC: 71521-392 | Form: CREAM
Manufacturer: Lavior Pharma Inc
Category: otc | Type: HUMAN OTC DRUG LABEL
Date: 20241022

ACTIVE INGREDIENTS: DIMETHICONE 1 g/100 g
INACTIVE INGREDIENTS: LAURYL LAURATE; GLYCERIN; CASTOR OIL; POTASSIUM SORBATE; LINALOOL, (+/-)-; CITRAL; XANTHAN GUM; ARACHIDYL GLUCOSIDE; PROPANEDIOL; ARACHIDYL ALCOHOL; DITTRICHIA VISCOSA WHOLE; DOCOSANOL; CARNAUBA WAX; CANDELILLA WAX; LIMONENE, (+)-; SODIUM BENZOATE; CARBOMER INTERPOLYMER TYPE A (55000 CPS); EDETATE DISODIUM; ORANGE OIL; LEUCONOSTOC/RADISH ROOT FERMENT FILTRATE; STEARYL ALCOHOL; CETYL ALCOHOL; SYNTHETIC BEESWAX

Active Ingredient

Dimethicone 1%..............................Skin Protectant

Purpose

Skin Protectant

Uses

Helps prevent and temporarily protects chafed, chapped, or cracked skin.

Warnings

For external use only.

When using this product

do not get into the eyes

Stop use and ask physician if

- condition worsens
- symptoms last more than 7 days or clear up and occur again within a few days

Do not use on

- deep or puncture wounds
- animal bites
- serious burns

Keep out of reach of children

If swallowed, get medical help or contact a Poison Control Center right away.

Directions

Apply as needed.

Other information

Store at 20° – 25°C (68° – 77°F).

Inactive Ingredients

Water, Propanediol, Ricinus Communis (Castor) Seed Oil, Lauryl Laurate, Arachidyl Alcohol, Inula Viscosa Flower/Leaf/Stem Extract, Stearyl Alcohol, Behenyl Alcohol, Glycerin, Synthetic Beeswax, Arachidyl Glucoside, Cetyl Alcohol, Copernicia Cerifera (Carnauba) Wax, Euphorbia Cerifera (Candelilla) Wax, Limonene, Sodium Benzoate, Acrylates/C10-30 Alkyl Acrylate Crosspolymer, Potassium Sorbate, Disodium EDTA, Xanthan Gum, Hydrolyzed Vegetable Protein, Citrus Aurantium Dulcis (Orange) Peel Oil, Leuconostoc/Radish Root Ferment Filtrate, Linalool, Citral

Questions?

Call toll free 1-844-474-2552 or visit www.lavior.com